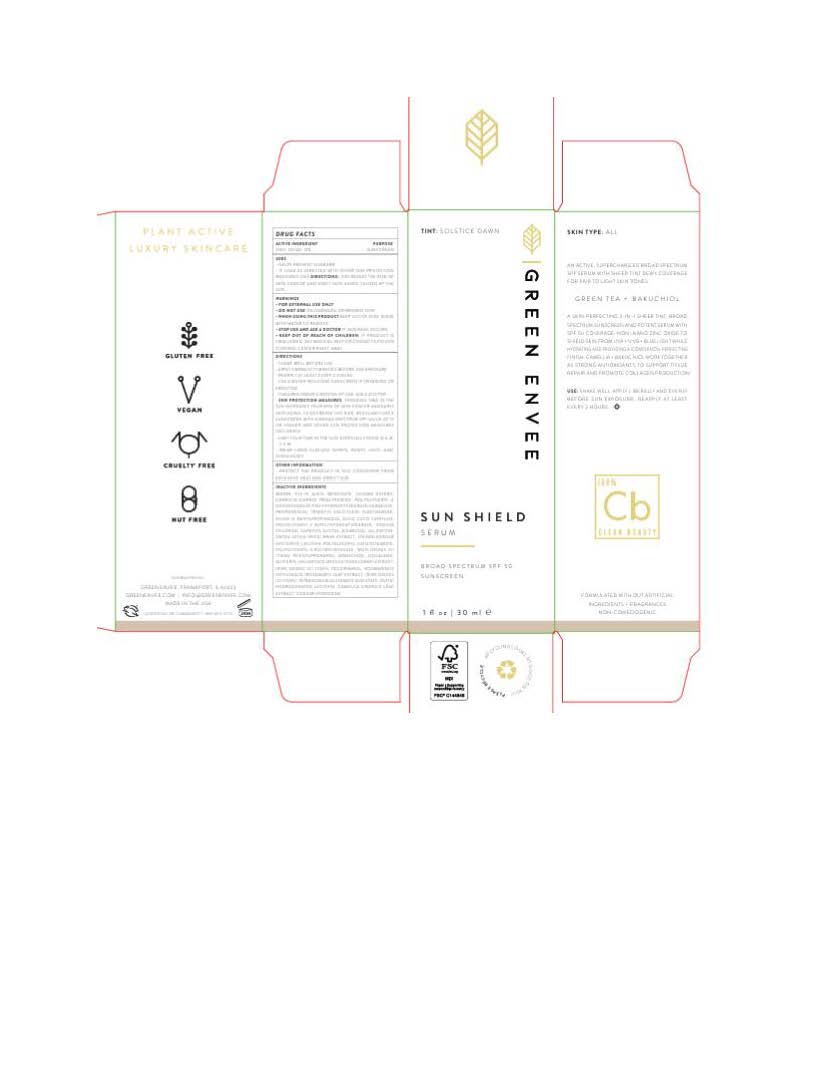 DRUG LABEL: Green Envee Radiance Sheer
NDC: 83678-2726 | Form: LOTION
Manufacturer: Green Envee
Category: otc | Type: HUMAN OTC DRUG LABEL
Date: 20251106

ACTIVE INGREDIENTS: ZINC OXIDE 132 mg/1 mL
INACTIVE INGREDIENTS: SQUALANE; BAKUCHIOL; SODIUM HYDROXIDE; ALKYL (C12-15) BENZOATE; ROSMARINUS OFFICINALIS FLOWER; TETRASODIUM GLUTAMATE DIACETATE; SODIUM CHLORIDE; POLYGLYCERYL-4 DIISOSTEARATE/POLYHYDROXYSTEARATE/SEBACATE; CAPRYLIC/CAPRIC TRIGLYCERIDE; TRIDECYL SALICYLATE; ORYZA SATIVA WHOLE; WATER; NIACINAMIDE; NYLON-12; COCO-CAPRYLATE; HYDROLYZED JOJOBA ESTERS; .ALPHA.-BISABOLOL, (+)-; PROPANEDIOL; LECITHIN, SOYBEAN; ALLANTOIN; SILICON DIOXIDE; TOCOPHEROL; CAPRYLYL GLYCOL; HELIANTHUS ANNUUS FLOWERING TOP; METHYLPROPANEDIOL; POLYGLYCERYL-2 DIPOLYHYDROXYSTEARATE; POLYGLYCERYL-3 DIISOSTEARATE; GLYCERIN; STEARALKONIUM HECTORITE; FERRIC OXIDE RED; CAMELLIA SINENSIS LEAF OIL; FERRIC OXIDE YELLOW; FERROSOFERRIC OXIDE; RUTIN

Green Envee Radiance Sheer